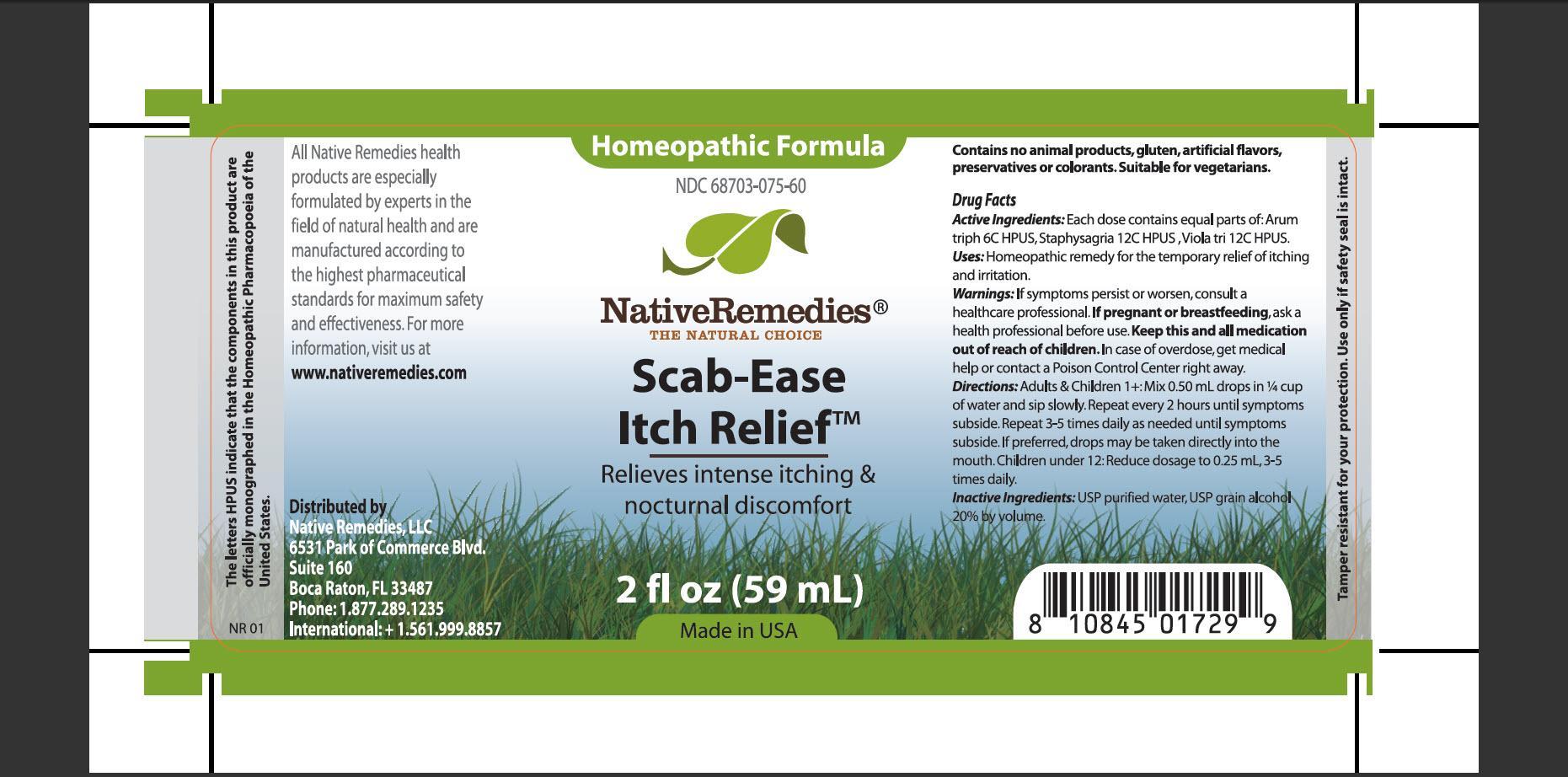 DRUG LABEL: Scab-Ease Itch Relief
NDC: 68703-075 | Form: TINCTURE
Manufacturer: Native Remedies, LLC
Category: homeopathic | Type: HUMAN OTC DRUG LABEL
Date: 20130320

ACTIVE INGREDIENTS: ARISAEMA TRIPHYLLUM ROOT 6 [hp_C]/1 mL; DELPHINIUM STAPHISAGRIA SEED 12 [hp_C]/1 mL; VIOLA TRICOLOR 12 [hp_C]/1 mL
INACTIVE INGREDIENTS: WATER; ALCOHOL

Scab-Ease Itch Relief

PURPOSE

Relieves intense itching and nocturnal discomfort

ACTIVE INGREDIENT

Active Ingredients:Each dose contains equal parts of: Arum triph 6C HPUS, Staphysagria 12C HPUS, Viola tri 12C HPUS

INDICATIONS AND USAGE

Uses: Homeopathic remedy for the temporary relief of itching and irritation

WARNINGS

Warnings: If symptoms persist or worsen, consult a healthcare professional

PREGNANCY OR BREAST FEEDING

If pregnant or breastfeeding, ask a health professional before use

KEEP OUT OF REACH OF CHILDREN

Keep this and all medication out of reach of children

OVERDOSAGE

In case of overdose, get medical help or contact a Poison Cneter right away

DOSAGE AND ADMINISTRATION

Directions: Adults and Children 1+: mix 0.50 mL drops in 1/4 cup of water and sip slowly. Repeat every 2 hours until symptoms subside. Repeat 3-5 times daily as needed until symptoms subside. If preferred, drop may be taken directly into the mouth. Children under 12: Reduce dosage to 0.25 mL, 3-5 times daily

INACTIVE INGREDIENT

Inactive Ingredients: UPS purified water, UPS grain alcohol 20% by volume

PATIENT COUNSELING INFORMATION

The letters HPUS indicate that the components in this product are officially monographed in the Homeopathic Pharmacopoeia of the United States

All Native Remedies health products are especially formulated by experts in the field of natural health and are manufactured according to the highest pharmaceutical standards for maximum safety and effectiveness. For more information, visit us at www.nativeremedies.com

Distributed by
Native Remedies, LLC
6531 Park of Commerce Blvd.
Suite 160
Boca Raton, Fl 33487
Phone: 1.877.289.1235
International: +1.561.999.8857

Contains no animal products, gluten, artificial flavors, preservatives or colorant. Suitable for vegetarians

STORAGE AND HANDLING

Tamper resistant for your protection. Use only if safety seal is intact.